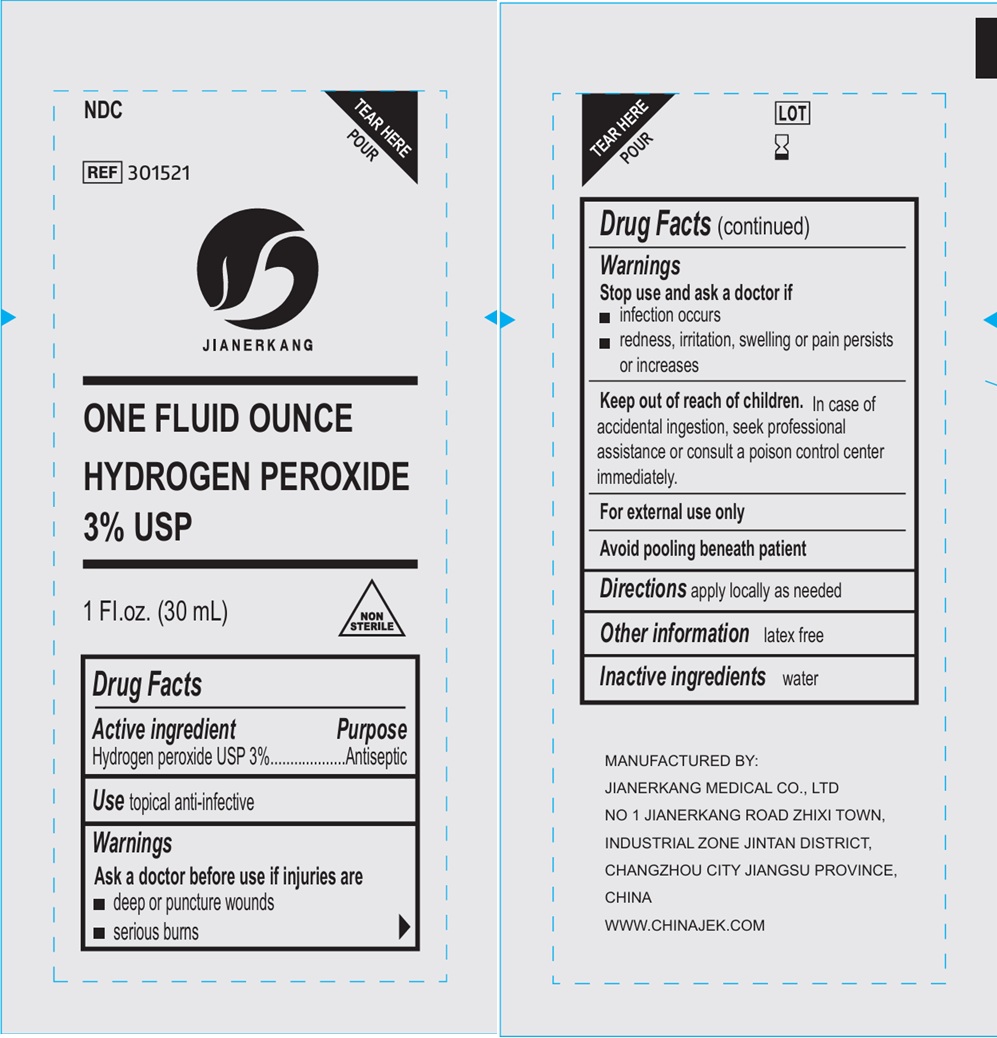 DRUG LABEL: Jianerkang One Fluid Ounce Hydrogen Peroxide
NDC: 34645-0028 | Form: SOLUTION
Manufacturer: Jianerkang Medical Co., Ltd
Category: otc | Type: HUMAN OTC DRUG LABEL
Date: 20250306

ACTIVE INGREDIENTS: HYDROGEN PEROXIDE 30 mg/1 mL
INACTIVE INGREDIENTS: WATER

Jianerkang One Fluid Ounce Hydrogen Peroxide

Active ingredient

Hydrogen peroxide USP 3%

Purpose

Antiseptic

Use

- topical anti-infective

Warnings

Ask a doctor before use if injuries are

Ask a doctor before use if injuries are

- deep or puncture wounds
- serious burns

Stop use and ask a doctor if

- infection occurs
- redness, irritation, swelling or pain persists or increases

Keep out of reach of children.

In case of accidental ingestion, seek professional assistance or consult a poison control center immediately.

Directions

- apply locally as needed

Other information

- latex free

Inactive ingredient

water